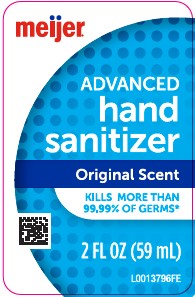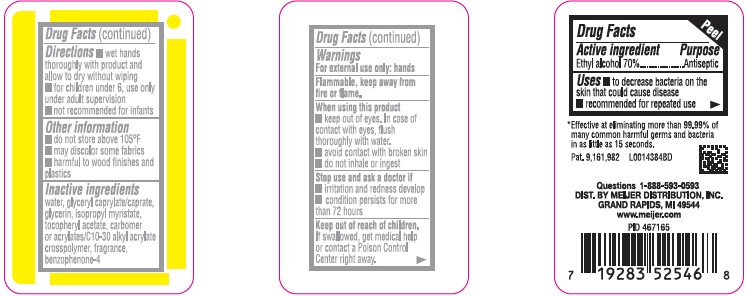 DRUG LABEL: Advanced Hand Sanitizer
NDC: 41250-370 | Form: GEL
Manufacturer: Meijer, Inc.
Category: otc | Type: HUMAN OTC DRUG LABEL
Date: 20260219

ACTIVE INGREDIENTS: ALCOHOL 70 mL/100 mL
INACTIVE INGREDIENTS: WATER; GLYCERYL CAPRYLATE/CAPRATE; GLYCERIN; ISOPROPYL MYRISTATE; .ALPHA.-TOCOPHEROL ACETATE; CARBOMER COPOLYMER TYPE A (ALLYL PENTAERYTHRITOL CROSSLINKED); SULISOBENZONE

Meijer 370.001/370AB-AE rev 1
Advanced Hand Sanitizer

Active ingredient

Ethyl Alcohol 70%

Purpose

Antiseptic

Use

- to decrease bacteria on the skin that could cause disease
- recommended for repeated use

Warnings

For external use only: hands

Flammable, keep away from fire or flame.

when using this product

- keep out of eyes. In case of contact with eyes, flush thoroughly with water.
- avoid contact with broken skin
- do not inhale or ingest

Stop use and ask a doctor if

- skin irritation and redness develop
- condition persists for more than 72 hours

Keep out of reach of children.

If swallowed, get medical help or contact a Poison Control Center right away.

Directions

- wet hands thoroughly with product and allow to dry without wiping
- for children under 6, use only under adult supervision
- not recommended for infants

Other information

- do not store above 105⁰F
- may discolor some fabrics
- harmful to wood finishes and plastics

Inactive ingredients

water, glyceryl caprylate/caprate, glycerin, isopropyl myristate, tocopheryl acetate, acrylates/C 10-30 alkyl acrylate crosspolymer, fragrance, benzophenone-4

Claim

*Effective at eliminating more that 99.99% of many common harmful germs and bacteria in as little as 15 seconds.

ADVERSE REACTION

Pat. 9, 161, 982

Questions 1-888-593-0593

DIST. BY MEIJER DISTRIBUTION, INC.

GRAND RAPIDS, MI 49544

www.meijer.com

principal display panel

meijer®

ADVANCED

Hand Sanitizer

Original Scent

KILLS MORE THAN 99.99% of germs*

2 FL OZ (59 mL)